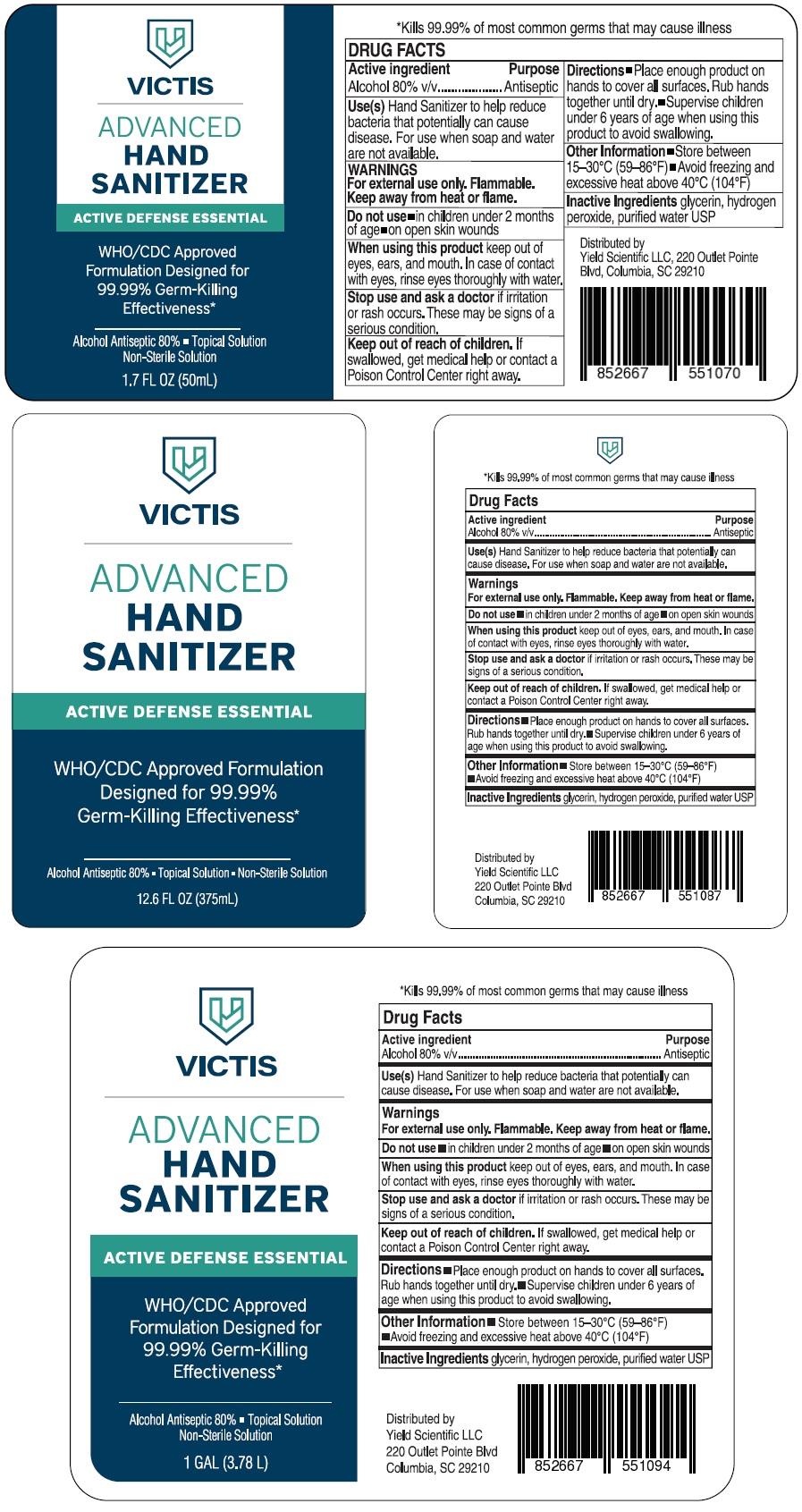 DRUG LABEL: Victis
NDC: 76803-180 | Form: SOLUTION
Manufacturer: Yield Scientific Llc
Category: otc | Type: HUMAN OTC DRUG LABEL
Date: 20200429

ACTIVE INGREDIENTS: ALCOHOL 80 mL/100 mL
INACTIVE INGREDIENTS: GLYCERIN; HYDROGEN PEROXIDE; WATER

VICTIS HAND SANITIZER ACTIVE DEFENSE ESSENTIAL

Active ingredient

Alcohol 80% v/v

Purpose

Antiseptic

Use(s)

Hand Sanitizer to help reduce bacteria that potentially can cause disease. For use when soap and water are not available.

Warnings

For external use only. Flammable. Keep away from heat or flame.

Do not use ▪ in children under 2 months of age ▪ on open skin wounds

When using this product keep out of eyes, ears, and mouth. In case of contact with eyes, rinse eyes thoroughly with water.

Stop use and ask a doctor if irritation or rash occurs. These may be signs of a serious condition.

Keep out of reach of children. If swallowed, get medical help or contact a Poison Control Centre right away.

DOSAGE AND ADMINISTRATION

Directions ▪ Place enough product on hands to cover all surfaces. Rub hands together until dry. ▪ Supervise children under 6 years of age when using this product to avoid swallowing.

Other Information ▪ Store between 15-30°C (59-86°F). ▪ Avoid Freezing and excessive heat above 40°C (104°F)

Inactive Ingredients glycerin, hydrogen peroxide, purified water USP

WHO/CDC Approved Formulation Designed for 99.99% Germ-Killing Effectiveness*

▪ Topical Solution ▪ Non-Sterile Solution

*Kills 99.99% of most common germs that may cause illness

Distributed by

Yield Scientific LLC, 220 Outlet Pointe

Blvd, Columbia, SC 29210